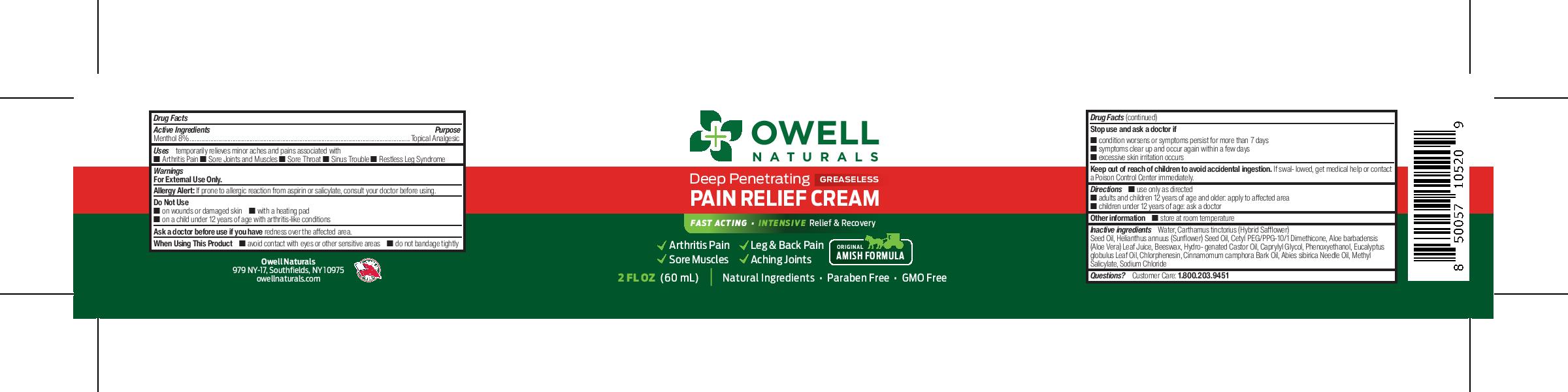 DRUG LABEL: Owell Naturals Pain Relief Cream
NDC: 83570-500 | Form: CREAM
Manufacturer: Owell Naturals Brand LLC
Category: otc | Type: HUMAN OTC DRUG LABEL
Date: 20240927

ACTIVE INGREDIENTS: MENTHOL 8 g/100 mL
INACTIVE INGREDIENTS: SUNFLOWER SEED OIL GLYCERETH-8 ESTERS; PEG-8 BEESWAX; CAPRYLYL GLYCOL; ABIES SIBIRICA LEAF OIL; WATER; CETYL PEG/PPG-10/1 DIMETHICONE (HLB 2); EUCALYPTUS GLOBULUS LEAF; CINNAMOMUM CAMPHORA WHOLE; SODIUM CHLORIDE; ALOE VERA LEAF; METHYL SALICYLATE; SAFFLOWER OIL; CHLORPHENESIN; HYDROGENATED CASTOR OIL; PHENOXYETHANOL

Owell Naturals Pain Relief Cream

ACTIVE INGREDIENT

Menthol 8%

PURPOSE

Topical Analgesic

INDICATIONS AND USAGE

Arthritis Pain, Sore Joints and Muscles, Sore Throat, Sinus Trouble, Restless Leg Syndrome

Warnings
For External Use Only.
Allergy Alert: If prone to allergic reaction from aspirin or salicylate, consult your doctor before using.
Do Not Use
■ on wounds or damaged skin ■ with a heating pad
■ on a child under 12 years of age with arthritis-like conditions
Ask a doctor before use if you have redness over the affected area.
When Using This Product ■ avoid contact with eyes or other sensitive areas ■ do not bandage tightly

Stop use and ask a doctor if
■ condition worsens or symptoms persist for more than 7 days
■ symptoms clear up and occur again within a few days
■ excessive skin irritation occurs
Keep out of reach of children to avoid accidental ingestion. If swal- lowed, get medical help or contact
a Poison Control Center immediately.

DOSAGE AND ADMINISTRATION

Directions ■ use only as directed
■ adults and children 12 years of age and older: apply to affected area
■ children under 12 years of age: ask a doctor

INACTIVE INGREDIENT

Inactive ingredients Water, Carthamus tinctorius (Hybrid Safflower) Seed Oil, Helianthus annuus (Sunflower) Seed Oil, Cetyl PEG/PPG-10/1 Dimethicone, Aloe barbadensis (Aloe Vera) Leaf Juice, Beeswax, Hydro- genated Castor Oil, Caprylyl Glycol, Phenoxyethanol, Eucalyptus globulus Leaf Oil, Chlorphenesin, Cinnamomum camphora Bark Oil, Abies sibirica Needle Oil, Methyl Salicylate, Sodium Chloride

Keep out of reach of children to avoid accidental ingestion. If swallowed, get medical help or contact a Poison Control Center immediately.